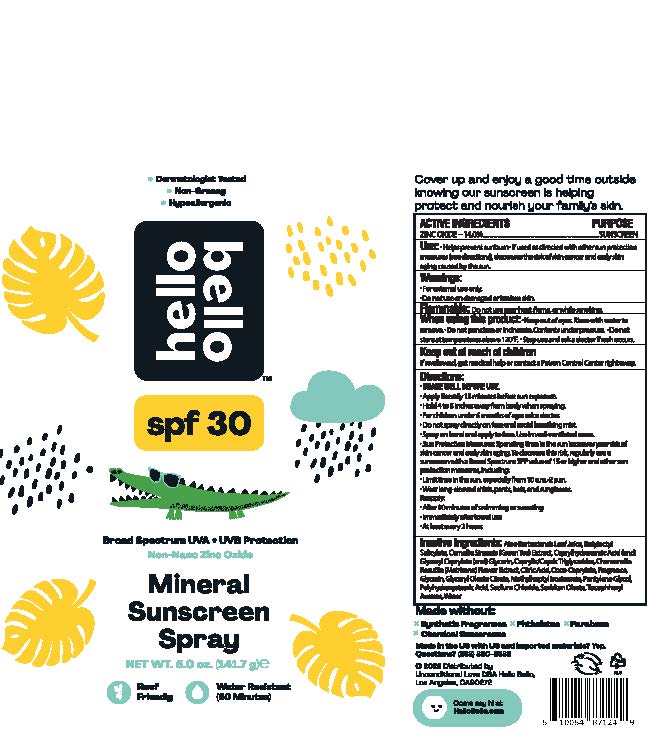 DRUG LABEL: Mineral Sunscreen SPF30
NDC: 73418-104 | Form: SPRAY
Manufacturer: Hello Bello
Category: otc | Type: HUMAN OTC DRUG LABEL
Date: 20230930

ACTIVE INGREDIENTS: ZINC OXIDE 140 mg/1 g
INACTIVE INGREDIENTS: CITRIC ACID MONOHYDRATE; PENTYLENE GLYCOL; GLYCERYL MONOOLEATE CITRATE; POLYHYDROXYSTEARIC ACID STEARATE; ALPHA-TOCOPHEROL ACETATE; WATER; BUTYLOCTYL SALICYLATE; GREEN TEA LEAF; GLYCERYL CAPRYLATE; SORBITAN MONOOLEATE; CAPRYLHYDROXAMIC ACID; CHAMOMILE; SODIUM CHLORIDE; METHYLHEPTYL ISOSTEARATE; COCO-CAPRYLATE; ALOE VERA LEAF; GLYCERIN; MEDIUM-CHAIN TRIGLYCERIDES

Mineral Sunscreen Spray SPF30

Active Ingredients

Zinc Oxide 14.0%

Purpose

Sunscreen

Uses

- Helps prevent sunburn
- If used as directed with other sun protection measures (see Directions), decreases the risk of skin cancer and early skin aging caused by the sun

Warnings

For external use only

Do not use on

broken or damaged skin

Flammable:

Do not use near heat, flame, or while smoking

When using this product

Keep out of eyes. Rinse with water to remove. Do not puncture or incinerate. Contents under pressure. Do not store at temperatures above 120F.

Stop use and ask a doctor if

rash occurs

Keep out of reach of children.

If swallowed, get medical help or contact a Poison Control Center right away

Directions

- Shake well before use
- Apply liberally 15 minutes before sun exposure
- Hold 4 to 6 inches away from body when spraying
- For children under 6 months of age, ask a doctor
- Do not spray directly on face and avoid breathing mist
- Spray on hand and apply to face. Use in well-ventilated areas
- Sun Protection Measures: Spending time in the sun can increase your risk of skin cancer and early skin aging. To decrease this risk, regularly use sunscreen with a Broad Spectrum SPF value of 15 or higher and other sun protection measures including: • Limit time in the sun, especially from 10a.m. - 2p.m. • Wear long-sleeved shirts, pants, hats and sunglasses
- Reapply:
- • after 80 minutes of swimming or sweating
- • immediately after towel use
- • at least every 2 hours

Inactive Ingredients

Aloe Barbadensis Leaf Juice, Butyloctyl Salicylate, Camellia Sinensis (Green Tea) Leaf Extract, Caprylhydroxamic Acid, Glyceryl Caprylate, Glycerin, Caprylic/Capric Triglycerides, Chamomilla Recutita (Matricaria) Flower Extract, Citric Acid, Coco-Caprylate, Fragrance, Glyceryl Oleate Citrate, Methylheptyl Isostearate, Pentylene Glycol, Polyhydroxystearic Acid, Sodium Chloride, Sorbitan Oleate, Tocopheryl Acetate, Water